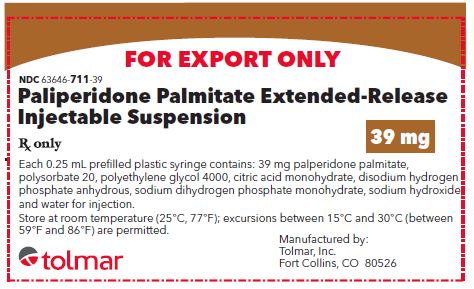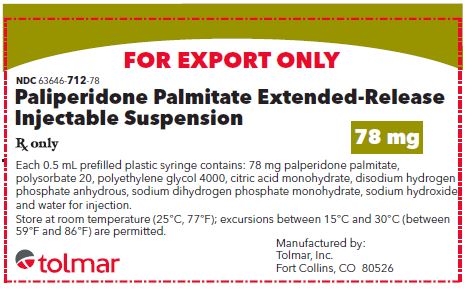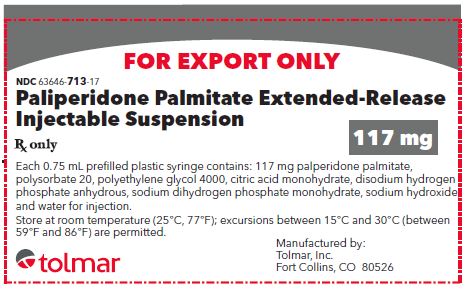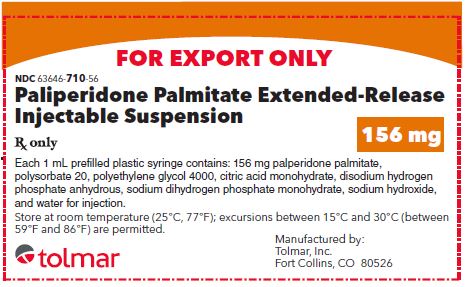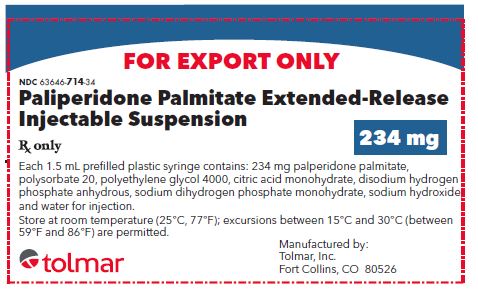 DRUG LABEL: Paliperidone Palmitate
NDC: 63646-711 | Form: KIT | Route: INTRAMUSCULAR
Manufacturer: TOLMAR Inc.
Category: prescription | Type: HUMAN PRESCRIPTION DRUG LABEL
Date: 20240109

ACTIVE INGREDIENTS: PALIPERIDONE PALMITATE 39 mg/0.25 mL
INACTIVE INGREDIENTS: POLYSORBATE 20; POLYETHYLENE GLYCOL 4000; CITRIC ACID MONOHYDRATE; SODIUM PHOSPHATE, DIBASIC, ANHYDROUS; SODIUM PHOSPHATE, MONOBASIC, UNSPECIFIED FORM; SODIUM HYDROXIDE; WATER

Paliperidone Palmitate Extended-Release Injectable Suspension